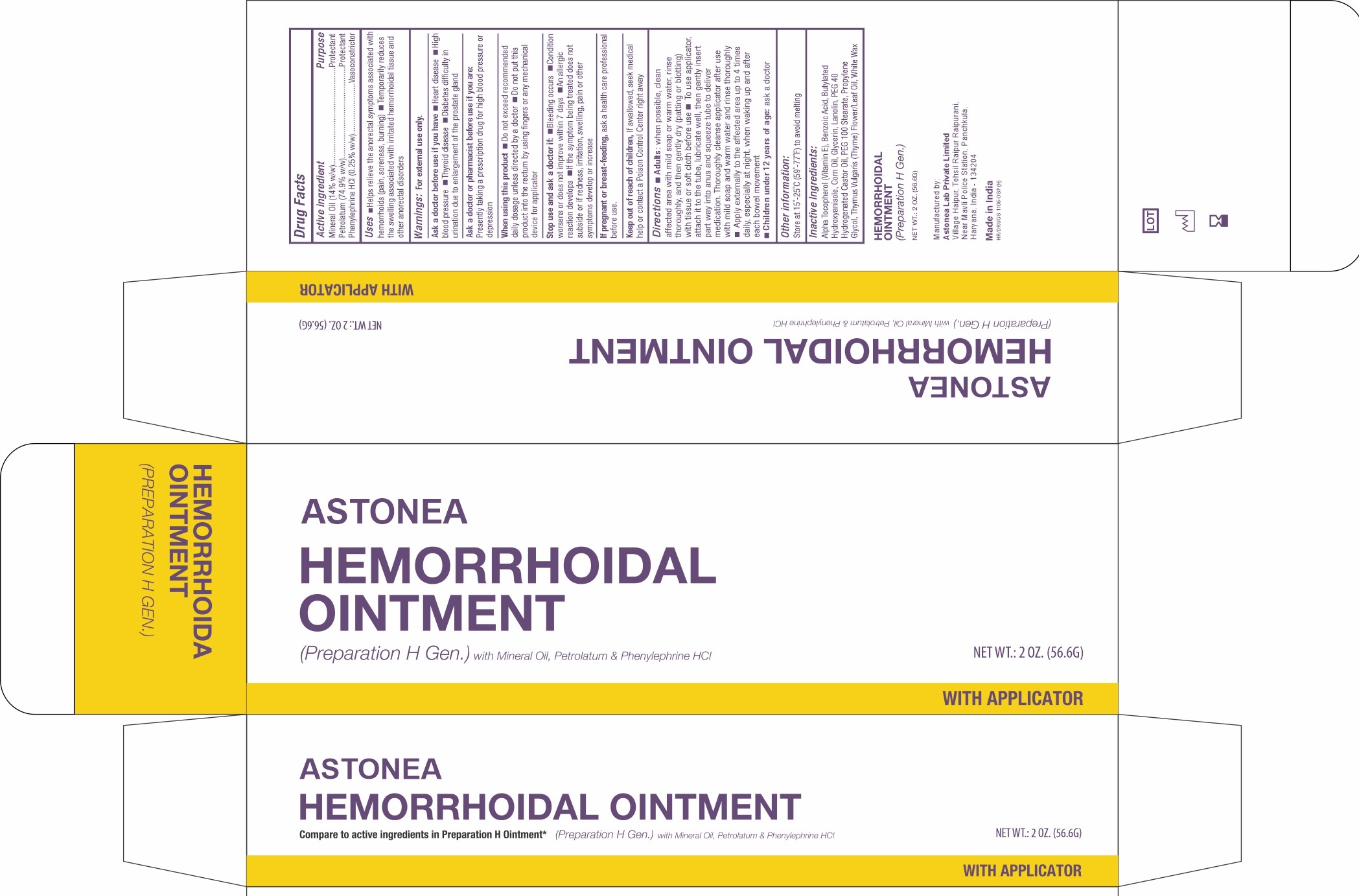 DRUG LABEL: HEMORRHOIDALCREAMPro
NDC: 77338-410 | Form: CREAM
Manufacturer: ASTONEA LABS PRIVATE LIMITED
Category: otc | Type: HUMAN OTC DRUG LABEL
Date: 20240625

ACTIVE INGREDIENTS: MINERAL OIL 14 g/100 g; PHENYLEPHRINE HYDROCHLORIDE 0.25 g/100 g; PETROLATUM 74.9 g/100 g
INACTIVE INGREDIENTS: POLYOXYL 100 STEARATE; PROPYLENE GLYCOL; WHITE WAX; THYMUS VULGARIS LEAF; BENZOIC ACID; .ALPHA.-TOCOPHEROL ACETATE; BUTYLATED HYDROXYANISOLE; CORN OIL; GLYCERIN; LANOLIN; POLYOXYL 40 HYDROGENATED CASTOR OIL

Astonea Hemorrhoidal Cream

Drug Facts

ACTIVE INGREDIENT

PURPOSE

Mineral Oil (14% w/w)............................................. Skin Protectant

Petrolatum (74.9% w/w)........................................... Skin Protectant

Phenylephrine HCl (0.25% w/w).................. Vasoconstrictor

Uses

- Helps relieve the anorectal symptoms associated with hemorrhoids (pain, soreness, burning)
- Temporarily reduces the swelling associated with irritated hemorrhoidal tissue and other anorectal disorders

Warnings

For external use only

Ask a doctor before use if you have

- heart disease
- high blood pressure
- thyroid disease
- diabetes
- difficulty in urination due to enlargement of the prostate gland

Ask a doctor or pharmacist before use if you are presently taking a prescription drug for high blood pressure or depression.

When using this product

- do not exceed the recommended daily dosage unless directed by a doctor
- do not put into the rectum by using fingers or any mechanical device or applicator

Stop use and ask a doctor if

- bleeding occurs
- condition worsens or does not improve within 7 days
- an allergic reaction develops
- the symptom being treated does not subside or if redness, irritation, swelling, pain, or other symptoms develop or increase

PREGNANCY OR BREAST FEEDING

If pregnant or breast-feeding, ask a health professional before use.

Keep out of reach of children. If swallowed, get medical help or contact a Poison Control Center right away.

Directions

- Adults: when possible, clean affected area with mild soap or warm water, rinse thoroughly, and then gently dry (patting or blotting) with tissue or soft cloth before use
- To use applicator, attach it to the tube, lubricate well, then gently insert part way into anus and squeeze tube to deliver medication. Thoroughly cleanse applicator after use with mild soap and warm water and rinse thoroughly
- Apply externally to the affected area up to 4 times daily, especially at night, when waking up and after each bowel movement
- Children under 12 years of age: ask a doctor

Other information

store at 20-25°C (68-77°F)

Inactive ingredients

Alpha Tocopherol (Vitamin E), Benzoic Acid, Butylated Hydroxyanisole, Corn Oil, Glycerin, Lanolin, PEG-40 Hydrogenated Castor Oil, PEG-100 Stearate, Propylene Glycol, Thymus Vulgaris (Thyme) Flower/Leaf Oil, White Wax